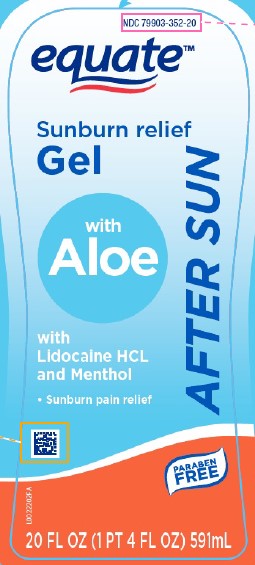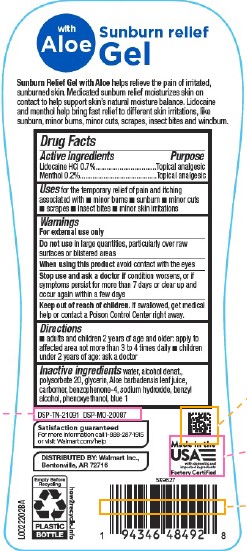 DRUG LABEL: Aloe Vera Gel
NDC: 79903-352 | Form: GEL
Manufacturer: Walmart Inc.
Category: otc | Type: HUMAN OTC DRUG LABEL
Date: 20260227

ACTIVE INGREDIENTS: LIDOCAINE HYDROCHLORIDE 7 mg/1 mL; MENTHOL 2 mg/1 mL
INACTIVE INGREDIENTS: WATER; ALCOHOL; POLYSORBATE 20; GLYCERIN; ALOE VERA LEAF JUICE; CARBOMER HOMOPOLYMER, UNSPECIFIED TYPE; SULISOBENZONE; SODIUM HYDROXIDE; BENZYL ALCOHOL; PHENOXYETHANOL; FD&C BLUE NO. 1

Equate 747.002/747AC
After Sun Gel with Aloe

Claims

with Aloe

Sunburn relief Gel

Sunburn Relief Gel with Aloe helps relieve the pain of irritated, sunburned skin. Medicated sunburn relief moisturizes skin on contact to help support skin's natural moisture balance. Lidocaine and menthol help bring fast relief to different skin irratations, like sunburn, minor burns, minor cuts, scrapes, insect bites and windburn.

Active ingredients

Lidocaine HCl 0.7%
Menthol 0.2%

Purpose

Topical analgesic

Uses

for the temporary relief of pain and itching associated with

- minor burns
- sunburn
- minor cuts
- scrapes
- insect bites
- minor skin irritations

Warnings

For external use only

Do not use

in large quantities, particularly over raw surfaces or blistered areas

When using this product

avoid contact with the eyes

Stop use and ask a doctor if

condition worsens, or if symptoms persist for more than 7 days or clear up and occur again within a few days

Keep out of reach of children.

If swallowed, get medical help or contact a Poison Control Center right away.

Directions

- adults and children 2 years of age and older: apply to affected area not more than 3 to 4 times daily
- children under 2 years of age: ask a doctor

Inactive ingredients

water, alcohol denat., polysorbate 20, glycerin, Aloe barbadensis leaf juice, carbomer, benzophenone-4, sodium hydroxide, benzyl alcohol, phenoxyethanol, blue 1

ADVERSE REACTION

DSP-TN-21091 DSP-MO-20087

Satisfaction guaranteed

For more information call 1-888-287-1915 or visit Walmart.com/help

DISTRIBUTED BY: Walmart Inc.,

Bentonville, AR 72716

Made in the USA with domestic and imported ingredients

Factory Certifited

Empty Before Recycling

PLASTIC BOTTLE

how2recycle.info

PRINCIPAL DISPLAY PANEL

NDC 79903-352-20

equate™

Sunburn relief

Gel

with Aloe

AFTER SUN

with Lidocaine HCL and Menthol

- Sunburn pain relief

PARABEN FREE

20 FL OZ (1 PT 4 FL OZ) 591 mL